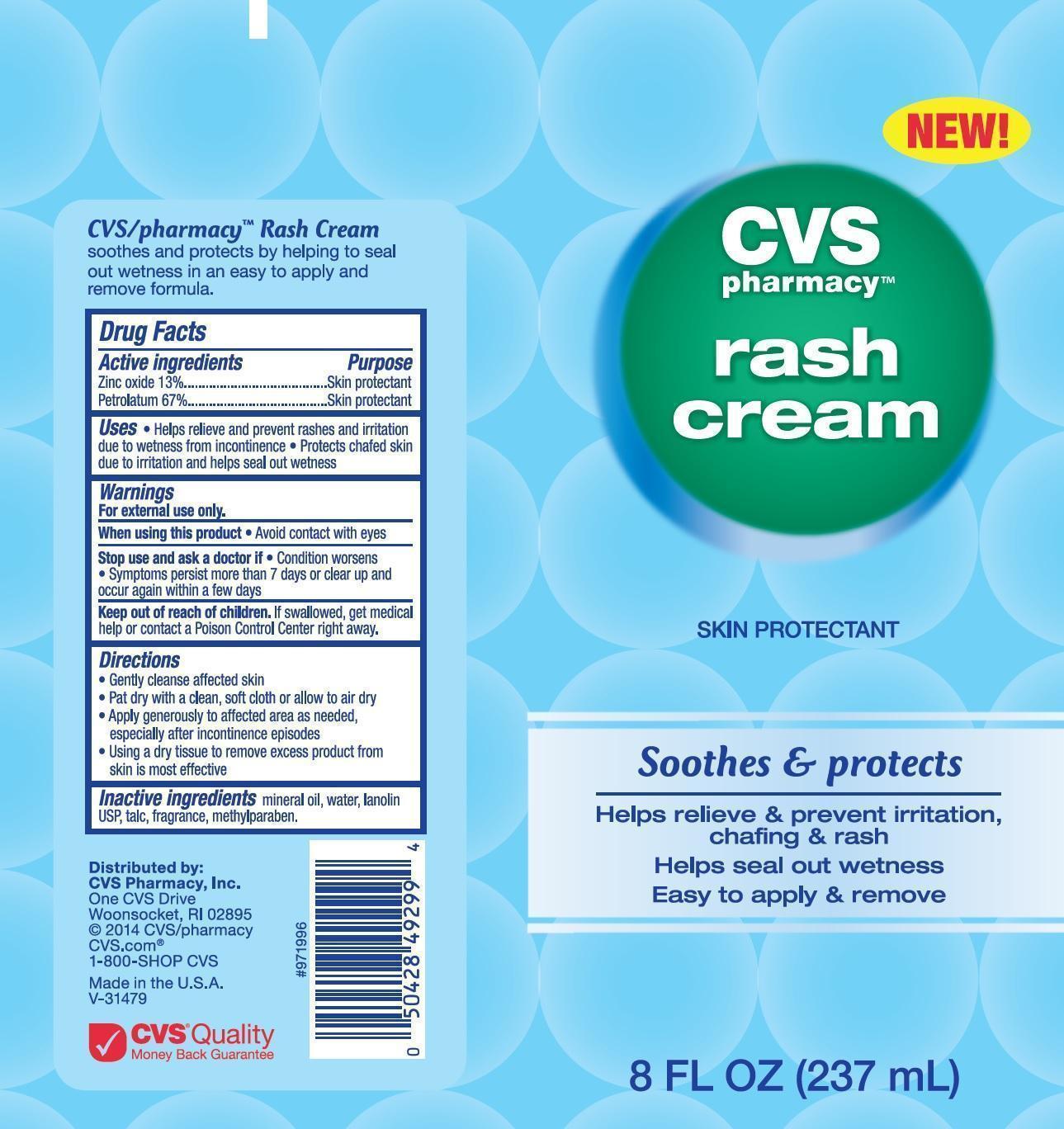 DRUG LABEL: CVS Pharmacy
NDC: 59779-988 | Form: CREAM
Manufacturer: CVS Pharmacy
Category: otc | Type: HUMAN OTC DRUG LABEL
Date: 20140520

ACTIVE INGREDIENTS: ZINC OXIDE 13 mg/1 mL; PETROLATUM 67 mg/1 mL
INACTIVE INGREDIENTS: MINERAL OIL; WATER; LANOLIN; TALC; METHYLPARABEN

CVS Pharmacy Rash Cream - Drug Facts

Active ingredients

Zinc oxide 13%

Petrolatum 67%

Purpose

Skin protectant

Use

- Helps relieve and prevent rashes and irritation due to wetness from incontinence
- Protects chafed skin due to irritation and helps seal out wetness

Warnings

For external use only.

When using this product

- Avoid contact with eyes

Stop use and ask a doctor if

- Condition worsens
- Symptoms persist more than 7 days or clear up and occur again within a few days

Keep out of reach of children.

If swallowed, get medical help or contact a Poison Control Center right away.

Directions

- Gently cleanse affected skin
- Pat dry with a clean, soft cloth or allow to air dry
- Apply generously to affected area as needed, especially after incontinence episodes
- Using a dry tissue to remove excess product from skin is most effective

Inactive ingredients

mineral oil, water, lanolin USP, talc, fragrance, methylparaben.

Distributed by: CVS Pharmacy, Inc.

One CVS Drive

Woonsocket, RI 02895

© 2014 CVS/pharmacy

CVS.com®

1-800-SHOP CVS

Made in the U.S.A.

CVS Pharmacy Rash Cream Zinc Oxide and Petrolatum Skin Protectant Label 8 FL OZ (237mL)

CVSRashCream8ozLabel.jpg